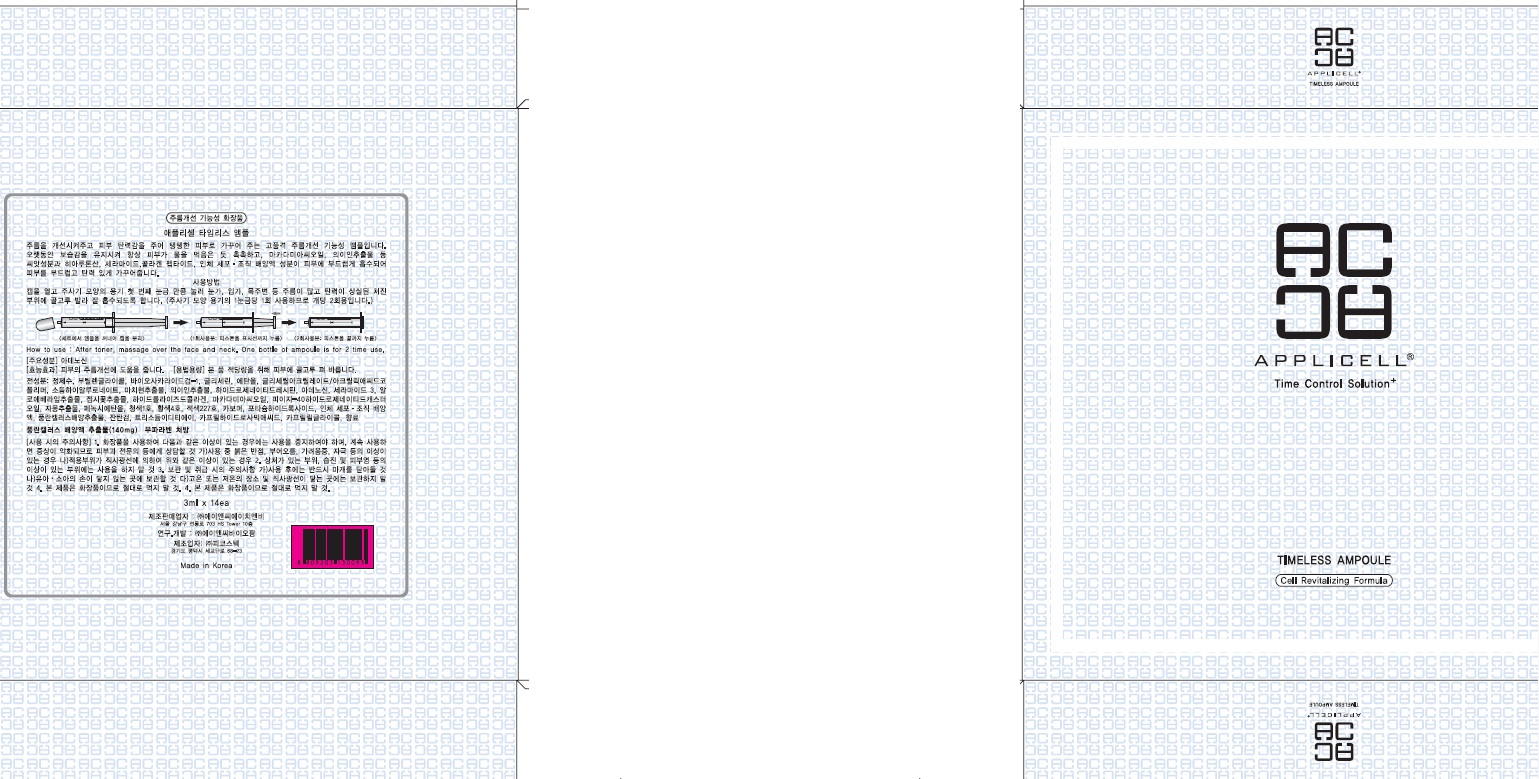 DRUG LABEL: Applicell Timeless Ampoule
NDC: 71098-060 | Form: SOLUTION
Manufacturer: Anc HnB Inc.
Category: otc | Type: HUMAN OTC DRUG LABEL
Date: 20161125

ACTIVE INGREDIENTS: Adenosine 1.2 mg/3 mL
INACTIVE INGREDIENTS: Water; Butylene Glycol

ACTIVE INGREDIENT

Active Ingredient: Adenosine 0.04%

INACTIVE INGREDIENT

Inactive Ingredients: Water, Butylene Glycol, Biosaccharide Gum-1, Glycerin, Alcohol, Glyceryl Acrylate/Acrylic Acid Copolymer, Sodium Hyaluronate, Portulaca Oleracea Extract, Coix Lacryma-Jobi Ma-yuen Seed Extract, Hydrogenated Lecithin, Ceramide 3, Aloe Barbadensis Leaf Extract, Althaea Rosea Flower Extract , Hydrolyzed Collagen, Macadamia Ternifolia Seed Oil, PEG-40 Hydrogenated Castor oil, Citrus Paradisi (Grapefruit) Fruit Extract, Phenoxyethanol, FD&C BLUE NO.1(CI 42090), FD&C YELLOW NO.5 (CI 19140), D&C RED NO.33 (CI 17200), Carbomer, Potassium Hydroxide, Human fibroblast Conditioned Media, Neofinetia Falcata Callus Culture Extract, Xanthan Gum, Trisodium EDTA, Caprylhydroxamic Acid, Caprylyl Glycol, Fragrance

PURPOSE

Purpose: Skin Protectant

WARNINGS

Warnings: For external use only When using this product do not get into eyes, Stop use and ask a doctor if rash occurs Do not use on - deep puncture wounds - animal bites - serious burns Keep out of reach of children

KEEP OUT OF REACH OF CHILDREN

INDICATIONS & USAGE

Indications & usage: APPLICELL Timeless Ampoule will improve skin wrinkle. And this ampoule will keep moist and elastic to the skin for a long time.

DOSAGE & ADMINISTRATION

How to use: After toner, massage over the face and neck. One bottle of ampoule is for 2 time use.